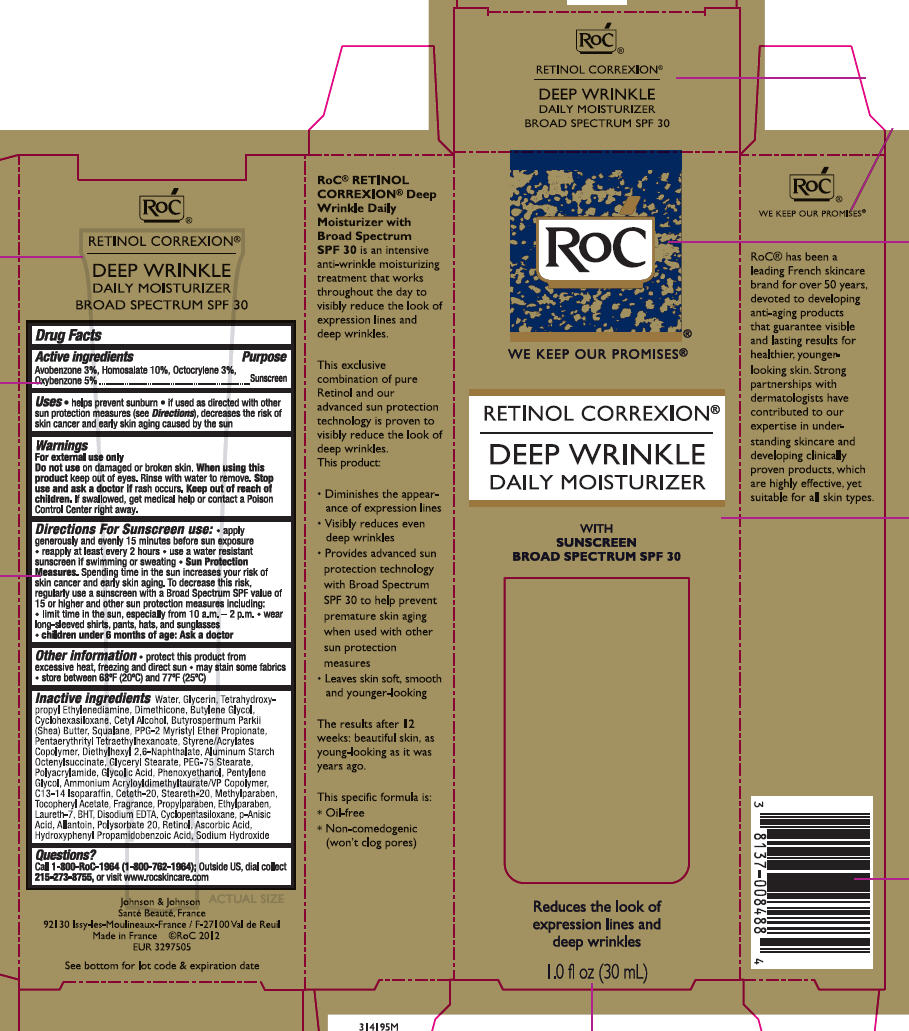 DRUG LABEL: Roc Retinol Correxion Deep Wrinkle Daily Moisturizer Sunscreen Broad Spectrum SPF 30
NDC: 73496-001 | Form: LOTION
Manufacturer: ROC Skincare
Category: otc | Type: HUMAN OTC DRUG LABEL
Date: 20191204

ACTIVE INGREDIENTS: AVOBENZONE 30 mg/1 mL; HOMOSALATE 100 mg/1 mL; OCTOCRYLENE 30 mg/1 mL; OXYBENZONE 50 mg/1 mL
INACTIVE INGREDIENTS: WATER; GLYCERIN; EDETOL; DIMETHICONE; BUTYLENE GLYCOL; CYCLOMETHICONE 6; CETYL ALCOHOL; SHEA BUTTER; SQUALENE; PPG-2 MYRISTYL ETHER PROPIONATE; PENTAERYTHRITYL TETRAETHYLHEXANOATE; STYRENE/ACRYLAMIDE COPOLYMER (500000 MW); DIETHYLHEXYL 2,6-NAPHTHALATE; ALUMINUM STARCH OCTENYLSUCCINATE; GLYCERYL MONOSTEARATE; PEG-75 STEARATE; POLYACRYLAMIDE (1500 MW); GLYCOLIC ACID; PHENOXYETHANOL; PENTYLENE GLYCOL; AMMONIUM ACRYLOYLDIMETHYLTAURATE/VP COPOLYMER; C13-14 ISOPARAFFIN; CETETH-20; STEARETH-20; METHYLPARABEN; ALPHA-TOCOPHEROL ACETATE; PROPYLPARABEN; ETHYLPARABEN; LAURETH-7; BUTYLATED HYDROXYTOLUENE; EDETATE DISODIUM ANHYDROUS; CYCLOMETHICONE 5; P-ANISIC ACID; ALLANTOIN; POLYSORBATE 20; RETINOL; ASCORBIC ACID; HYDROXYPHENYL PROPAMIDOBENZOIC ACID; SODIUM HYDROXIDE

Roc Retinol Correxion Deep Wrinkle Daily Moisturizer Sunscreen Broad Spectrum SPF 30

PACKAGE LABEL PRINCIPAL DISPLAY PANEL

OTC - PURPOSE

Active ingredientsPurposeAvobenzone (3%)SunscreenHomosalate (10%)SunscreenOctocrylene (3%)SunscreenOxybenzone (5%)Sunscreen ROC

OTC - KEEP OUT OF REACH OF CHILDREN

Keep out of reach of children. If swallowed, get medical help or contact a Poison Control Center right away

USES

Helps prevent sunburnif used as directed with other sun protection measures (see Directions), decreases the risk of skin cancer and early skin aging caused by the sun

WARNINGS

For external use only

Do not use on damaged or broken skin

When using this product keep out of eyes. Rinse with water to remove.

Stop use and ask a doctor if rash occurs

DIRECTIONS

For sunscreen use:apply generously and evenly15 minutes before sun exposurereapply at least every 2 hoursuse a water resistant sunscreen if swimming or sweatingSun Protection Measures. Spending time in the sun increases your risk of skin cancer and early skin aging. To decrease this risk, regularly use a sunscreen with a Broad Spectrum SPF value of 15 or higher and other sun protection measures including:limit time in the sun, especially from 10 a.m. – 2 p.m.wear long-sleeved shirts, pants, hats, and sunglasseschildren under 6 months of age: Ask a doctor

INACTIVE INGREDIENTS

Water, Glycerin, Tetrahydroxypropyl Ethylenediamine, Dimethicone, Butylene Glycol, Cyclohexasiloxane, Cetyl Alcohol, Butyrospermum Parkii (Shea) Butter, Squalane, PPG-2 Myristyl Ether Propionate, Pentaerythrityl Tetraethylhexanoate, Styrene/Acrylates Copolymer, Diethylhexyl 2,6-Naphthalate, Aluminum Starch Octenylsuccinate, Glyceryl Stearate, PEG-75 Stearate, Polyacrylamide, Glycolic Acid, Phenoxyethanol, Pentylene Glycol, Ammonium Acryloyldimethyltaurate/VP Copolymer, C13-14 Isoparaffin, Ceteth-20, Steareth-20, Methylparaben, Tocopheryl Acetate, Fragrance, Propylparaben, Ethylparaben, Laureth-7, BHT, Disodium EDTA, Cyclopentasiloxane, p-Anisic Acid, Allantoin, Polysorbate 20, Retinol, Ascorbic Acid, Hydroxyphenyl Propamidobenzoic Acid, Sodium Hydroxide

QUESTIONS?

Call 1-800-RoC-1964 (1-800-762-1964); Outside US, dial collect 215-273-8755, or visit ww.rocskincare.com